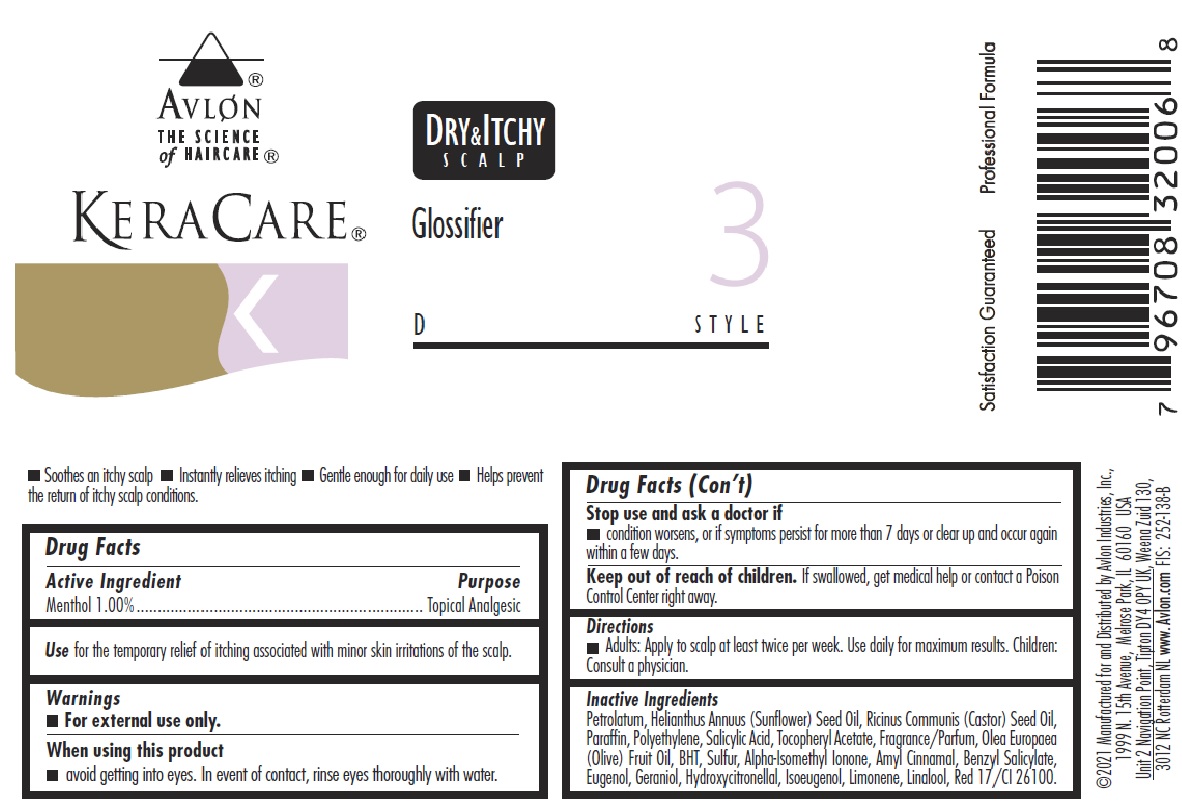 DRUG LABEL: KERACARE
NDC: 63766-001 | Form: GEL
Manufacturer: Avlon Industries, Inc.
Category: otc | Type: HUMAN OTC DRUG LABEL
Date: 20241009

ACTIVE INGREDIENTS: MENTHOL 10 mg/1 g
INACTIVE INGREDIENTS: PETROLATUM; SUNFLOWER OIL; CASTOR OIL; PARAFFIN; HIGH DENSITY POLYETHYLENE; SALICYLIC ACID; .ALPHA.-TOCOPHEROL ACETATE; BUTYLATED HYDROXYTOLUENE; SULFUR; OLIVE OIL; ISOMETHYL-.ALPHA.-IONONE; .ALPHA.-AMYLCINNAMALDEHYDE; BENZYL SALICYLATE; EUGENOL; GERANIOL; HYDROXYCITRONELLAL; ISOEUGENOL; LIMONENE, (+/-)-; LINALOOL, (+/-)-; D&C RED NO. 17

KeraCare Dry & Itchy Scalp Glossifier

ACTIVE INGREDIENT

Menthol 1.00%

PURPOSE

Topical Analgesic

USE

for the temporary relief of itching associated with minor skin irritations of the scalp.

WARNINGS

for external use only

When using this product

avoid getting into eyes. In event of contact, rinse eyes thoroughly with water.

Stop use and ask a doctor if

condition worsens, or if symptoms persist for more than 7 days or clear up and occur again within a few days.

Keep out of reach of children.

If swallowed, get medical help or contact a Poison Control Center right away.

Directions

Adults: Apply to scalp at least twice per week. Use daily for maximum results. Children: Consult a physician.

INACTIVE INGREDIENTS

Petrolatum, Helianthus Annuus (Sunflower) Seed Oil, Ricinus Communis (Castor) Seed Oil, Paraffin, Polyethylene, Salicylic Acid, Tocopheryl Acetate, Fragrance/Parfum, Olea Europaea (Olive) Fruit Oil, BHT, Sulfur, Alpha-Isomethyl Ionone, Amyl Cinnamal, Benzyl Salicylate, Eugenol, Geraniol, Hydroxycitronellal, Isoeugenol, Limonene, Linalool, Red 17/CI 26100.

PACKAGE LABEL

KeraCare Glossifier

Product NDC 63766-001